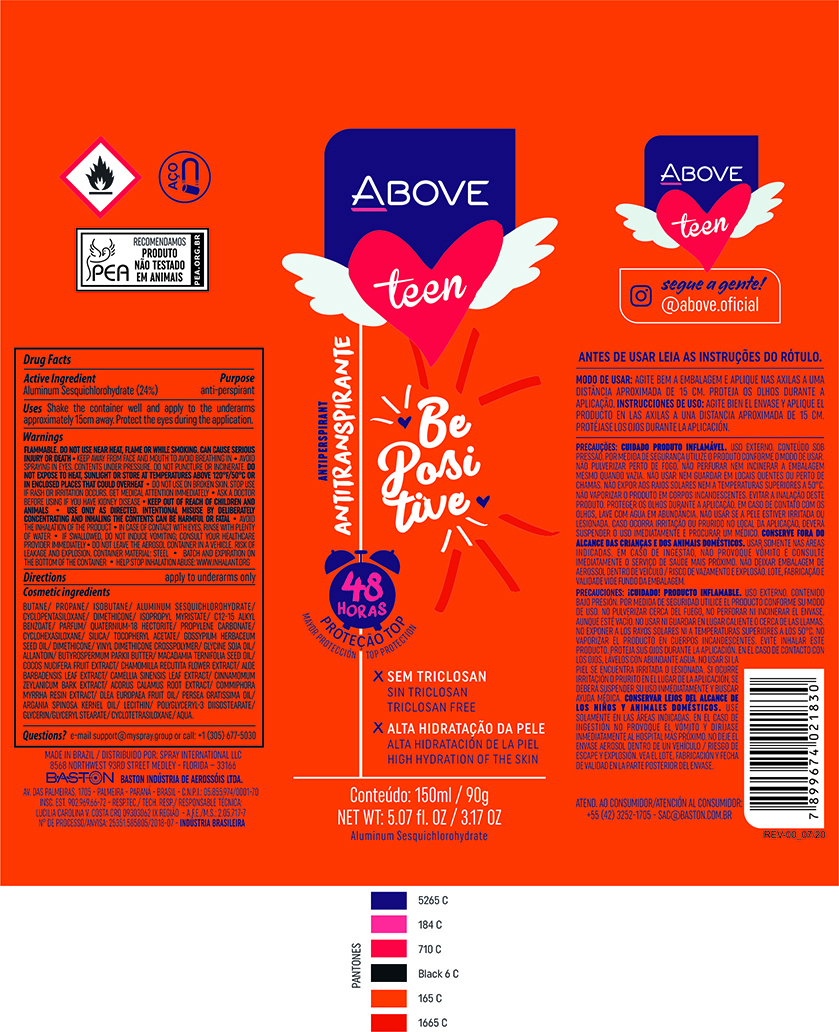 DRUG LABEL: Antiperspirant Above Teen Be Positive
NDC: 73306-1108 | Form: AEROSOL, SPRAY
Manufacturer: Baston Industria de Aerossóis Ltda
Category: otc | Type: HUMAN OTC DRUG LABEL
Date: 20241226

ACTIVE INGREDIENTS: ALUMINUM SESQUICHLOROHYDRATE 24 g/100 g
INACTIVE INGREDIENTS: GLYCERYL MONOSTEARATE; MACADAMIA OIL; POLYGLYCERYL-3 DIISOSTEARATE; COCONUT; GLYCERIN; LEVANT COTTON SEED; SILICA DIMETHYL SILYLATE; .ALPHA.-TOCOPHEROL ACETATE; ACORUS CALAMUS ROOT; ALLANTOIN; CHAMOMILE; PROPANE; ARGAN OIL; VINYL DIMETHICONE/METHICONE SILSESQUIOXANE CROSSPOLYMER; MYRRH OIL; ALOE VERA LEAF; DIMETHICONE; BUTANE; ISOBUTANE; LECITHIN, SOYBEAN; DISTEARDIMONIUM HECTORITE; WATER; ISOPROPYL MYRISTATE; AVOCADO OIL; GREEN TEA LEAF; CINNAMON BARK OIL; CYCLOMETHICONE 5; SHEA BUTTER; PROPYLENE CARBONATE

Antiperspirant Above Teen Be Positive Aerosol